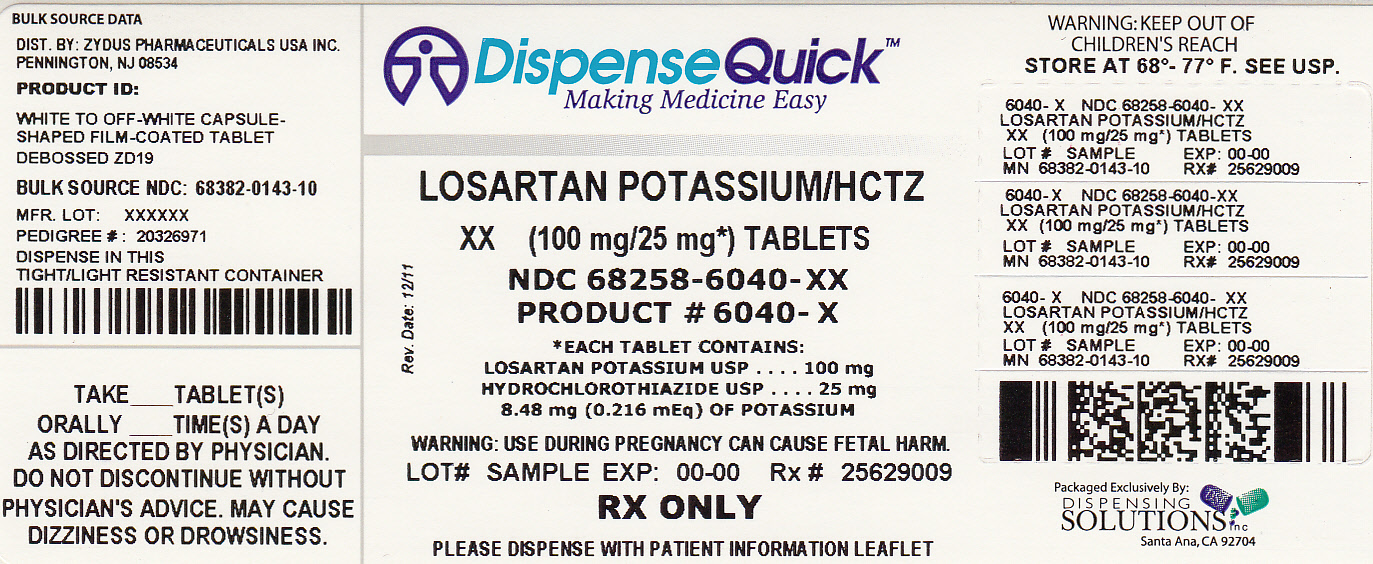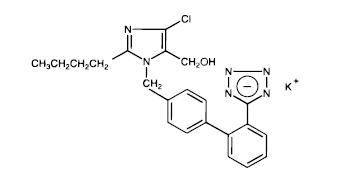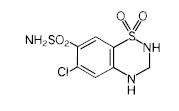 DRUG LABEL: LOSARTAN POTASSIUM AND HYDROCHLOROTHIAZIDE
NDC: 68258-6040 | Form: TABLET, FILM COATED
Manufacturer: Dispensing Solutions, Inc.
Category: prescription | Type: HUMAN PRESCRIPTION DRUG LABEL
Date: 20120220

ACTIVE INGREDIENTS: HYDROCHLOROTHIAZIDE 25 mg/1 1; LOSARTAN POTASSIUM 100 mg/1 1
INACTIVE INGREDIENTS: HYPROMELLOSES; LACTOSE MONOHYDRATE; MAGNESIUM STEARATE; POLYETHYLENE GLYCOL; SODIUM STARCH GLYCOLATE TYPE A POTATO; TALC; TITANIUM DIOXIDE; SILICON DIOXIDE; CELLULOSE, MICROCRYSTALLINE; HYDROXYPROPYL CELLULOSE, LOW SUBSTITUTED; STARCH, CORN

Losartan Potassium and Hydrochlorothiazide Tablets, USP

BOXED WARNING

USE IN PREGNANCY

When used in pregnancy during the second and third trimesters, drugs that act directly on the renin-angiotensin system can cause injury and even death to the developing fetus. When pregnancy is detected, losartan potassium and hydrochlorothiazide tablets should be discontinued as soon as possible (see WARNINGS, Fetal/Neonatal Morbidity and Mortality).

DESCRIPTION

Losartan potassium and hydrochlorothiazide tablets 50 mg/ 12.5 mg and losartan potassium and hydrochlorothiazide tablets 100 mg/ 25 mg combine an angiotensin II receptor (type AT1) antagonist and a diuretic, hydrochlorothiazide.

Losartan potassium, a non-peptide molecule, is chemically described as 2-butyl-4-chloro-1-[p-(o-1H-tetrazol-5-ylphenyl)benzyl]imidazole-5-methanol monopotassium salt. Its molecular formula is C22H22ClKN6O, and its structural formula is:

Losartan potassium, USP is off-white to creamish-yellow powder with a molecular weight of 461.01. It is soluble in water.

Oxidation of the 5-hydroxymethyl group on the imidazole ring results in the active metabolite of losartan.

Hydrochlorothiazide is 6-chloro-3,4-dihydro-2H-1,2,4-benzothiadiazine-7-sulfonamide 1,1-dioxide. Its molecular formula is C7H8ClN3O4S2 and its structural formula is:

Hydrochlorothiazide, USP is a white or practically white, practically odorless crystalline powder with a molecular weight of 297.74. It is slightly soluble in water; freely soluble in sodium hydroxide solution, in n-butylamine, and in dimethylformamide, sparingly soluble in methanol; insoluble in ether, in chloroform, and in dilute mineral acids.

Each losartan potassium and hydrochlorothiazide tablet intended for oral administration contains losartan potassium, 50 mg or 100 mg and hydrochlorothiazide, 12.5 mg or 25 mg. In addition, each tablet also contains the following inactive ingredients: colloidal silica anhydrous, hydroxypropyl cellulose (low substituted), hydroxypropyl methylcellulose, lactose monohydrate, magnesium stearate, maize starch, microcrystalline cellulose, polyethylene glycol, sodium starch glycolate, talc and titanium dioxide.

Losartan potassium and hydrochlorothiazide tablet 50 mg/ 12.5 mg contains 4.24 mg (0.108 mEq) of potassium and losartan potassium and hydrochlorothiazide tablet 100 mg/ 25 mg contains 8.48 mg (0.216 mEq) of potassium.

CONTRAINDICATIONS

Losartan potassium and hydrochlorothiazide tablets are contraindicated in patients who are hypersensitive to any component of this product.

Because of the hydrochlorothiazide component, this product is contraindicated in patients with anuria or hypersensitivity to other sulfonamide-derived drugs.

ADVERSE REACTIONS

Losartan potassium and hydrochlorothiazide has been evaluated for safety in 858 patients treated for essential hypertension and 3889 patients treated for hypertension and left ventricular hypertrophy. In clinical trials with losartan potassium and hydrochlorothiazide, no adverse experiences peculiar to this combination have been observed. Adverse experiences have been limited to those that were reported previously with losartan potassium and/or hydrochlorothiazide. The overall incidence of adverse experiences reported with the combination was comparable to placebo.

In general, treatment with losartan potassium and hydrochlorothiazide was well tolerated. For the most part, adverse experiences have been mild and transient in nature and have not required discontinuation of therapy. In controlled clinical trials, discontinuation of therapy due to clinical adverse experiences was required in only 2.8% and 2.3% of patients treated with the combination and placebo, respectively.

In these double-blind controlled clinical trials, the following adverse experiences reported with losartan-hydrochlorothiazide occurred in ≥1 percent of patients, and more often on drug than placebo, regardless of drug relationship:

 | Losartan Potassium and Hydrochlorothiazide (n=858) | Placebo (n=173)
Body as a Whole Abdominal pain Edema/swelling | 1.2 1.3 | 0.6 1.2
Cardiovascular Palpitation | 1.4 | 0.0
Musculoskeletal Back pain | 2.1 | 0.6
Nervous/Psychiatric Dizziness | 5.7 | 2.9
Respiratory Cough Sinusitis Upper respiratory infection | 2.6 1.2 6.1 | 2.3 0.6 4.6
Skin Rash | 1.4 | 0.0

The following adverse events were also reported at a rate of 1 % or greater, but were as, or more, common in the placebo group in studies of essential hypertension: asthenia/fatigue, diarrhea, nausea, headache, bronchitis, pharyngitis.

Adverse events occurred at about the same rates in men and women. Adverse events were somewhat more frequent in the elderly compared to non-elderly patients and somewhat more frequent in Blacks compared to non-Blacks for both the losartan and hydrochlorothiazide and the control groups.

A patient with known hypersensitivity to aspirin and penicillin, when treated with losartan potassium, was withdrawn from study due to swelling of the lips and eyelids and facial rash, reported as angioedema, which returned to normal 5 days after therapy was discontinued.

Superficial peeling of palms and hemolysis were reported in one subject treated with losartan potassium.

Losartan Potassium:

Other adverse experiences that have been reported with losartan, without regard to causality, are listed below:

Body as a Whole: Chest pain, facial edema, fever, orthostatic effects, syncope;

Cardiovascular: Angina pectoris, arrhythmias including atrial fibrillation, sinus bradycardia, tachycardia, ventricular tachycardia and ventricular fibrillation, CVA, hypotension, myocardial infarction, second degree AV block;

Digestive: Anorexia, constipation, dental pain, dry mouth, dyspepsia, flatulence, gastritis, vomiting;

General disorders and administration site conditions: malaise

Hematologic: Anemia;

Metabolic: Gout;

Musculoskeletal: Arm pain, arthralgia, arthritis, fibromyalgia, hip pain, joint swelling, knee pain, leg pain, muscle cramps, muscle weakness, musculoskeletal pain, myalgia, shoulder pain, stiffness;

Nervous System/Psychiatric: Anxiety, anxiety disorder, ataxia, confusion, depression, dream abnormality, hypesthesia, insomnia, libido decreased, memory impairment, migraine, nervousness, panic disorder, paresthesia, peripheral neuropathy, sleep disorder, somnolence, tremor, vertigo;

Respiratory: Dyspnea, epistaxis, nasal congestion, pharyngeal discomfort, respiratory congestion, rhinitis, sinus disorder;

Skin: Alopecia, dermatitis, dry skin, ecchymosis, erythema, flushing, photosensitivity, pruritus, sweating, urticaria;

Special Senses: Blurred vision, burning/stinging in the eye, conjunctivitis, decrease in visual acuity, taste perversion, tinnitus;

Urogenital: Impotence, nocturia, urinary frequency, urinary tract infection.

Hydrochlorothiazide:

Other adverse experiences that have been reported with hydrochlorothiazide, without regard to causality, are listed below:

Body as a Whole: Weakness;

Digestive: Pancreatitis, jaundice (intrahepatic cholestatic jaundice), sialadenitis, cramping, gastric irritation;

Hematologic: Aplastic anemia, agranulocytosis, leukopenia, hemolytic anemia, thrombocytopenia;

Hypersensitivity: Purpura, photosensitivity, urticaria, necrotizing angiitis (vasculitis and cutaneous vasculitis), fever, respiratory distress including pneumonitis and pulmonary edema;

Metabolic: Hyperglycemia, glycosuria, hyperuricemia;

Musculoskeletal: Muscle spasm;

Nervous System/Psychiatric: Restlessness;

Renal: Renal failure, renal dysfunction, interstitial nephritis;

Skin: Erythema multiforme including Stevens-Johnson syndrome, exfoliative dermatitis including toxic epidermal necrolysis;

Special Senses: Transient blurred vision, xanthopsia.

Persistent dry cough (with an incidence of a few percent) has been associated with ACE-inhibitor use and in practice can be a cause of discontinuation of ACE-inhibitor therapy. Two prospective, parallel-group, double-blind, randomized, controlled trials were conducted to assess the effects of losartan on the incidence of cough in hypertensive patients who had experienced cough while receiving ACE-inhibitor therapy. Patients who had typical ACE-inhibitor cough when challenged with lisinopril, whose cough disappeared on placebo, were randomized to losartan 50 mg, lisinopril 20 mg, or either placebo (one study, n=97) or 25 mg hydrochlorothiazide (n=135). The double-blind treatment period lasted up to 8 weeks. The incidence of cough is shown below.

Study 1† HCTZ Losartan Lisinopril

Cough 25% 17% 69%

Study 2†† Placebo Losartan Lisinopril

Cough 35% 29% 62%

† Demographics = (89% caucasian, 64% female)

†† Demographics = (90% caucasian, 51% female)

These studies demonstrate that the incidence of cough associated with losartan therapy, in a population that all had cough associated with ACE-inhibitor therapy, is similar to that associated with hydrochlorothiazide or placebo therapy.

Cases of cough, including positive re-challenges, have been reported with the use of losartan in post-marketing experience.

Severe Hypertension:

In a clinical study in patients with severe hypertension (SiDBP ≥110 mmHg), the overall pattern of adverse events reported through six weeks of follow-up was similar in patients treated with losartan potassium and hydrochlorothiazide tablets as initial therapy and in patients treated with losartan as initial therapy. There were no reported cases of syncope in either treatment group. There were 2 (0.6%) and 0 (0.0%) cases of hypotension reported in the group treated with losartan potassium and hydrochlorothiazide tablets and the group treated with losartan, respectively. There were 3 (0.8%) and 2 (1.2%) cases of increased serum creatinine (>0.5 mg/dL) in the group treated with losartan potassium and hydrochlorothiazide tablets and the group treated with losartan, respectively, during the same time period (see CLINICAL PHARMACOLOGY, Pharmacodynamics and Clinical Effects, Severe Hypertension).

Post-Marketing Experience:

The following additional adverse reactions have been reported in post-marketing experience:

Digestive: Hepatitis has been reported rarely in patients treated with losartan.

Hemic: Thrombocytopenia.

Hypersensitivity: Angioedema, including swelling of the larynx and glottis, causing airway obstruction and/or swelling of the face, lips, pharynx, and/or tongue has been reported rarely in patients treated with losartan; some of these patients previously experienced angioedema with other drugs including ACE inhibitors. Vasculitis, including Henoch-Schonlein purpura, has been reported with losartan. Anaphylactic reactions have been reported.

Metabolic and Nutrition: Hyperkalemia, hyponatremia have been reported with losartan.

Musculoskeletal: Rare cases of rhabdomyolysis have been reported in patients receiving angiotensin II receptor blockers.

Respiratory: Dry cough (see above) has been reported with losartan.

Skin: Erythroderma has been reported with losartan.

Laboratory Test Findings:

In controlled clinical trials, clinically important changes in standard laboratory parameters were rarely associated with administration of losartan potassium and hydrochlorothiazide tablets.

Creatinine, Blood Urea Nitrogen:

Minor increases in blood urea nitrogen (BUN) or serum creatinine were observed in 0.6 and 0.8 percent, respectively, of patients with essential hypertension treated with losartan potassium and hydrochlorothiazide tablets alone. No patient discontinued taking losartan potassium and hydrochlorothiazide tablets due to increased BUN. One patient discontinued taking losartan potassium and hydrochlorothiazide tablets due to a minor increase in serum creatinine.

Hemoglobin and Hematocrit:

Small decreases in hemoglobin and hematocrit (mean decreases of approximately 0.14 grams percent and 0.72 volume percent, respectively) occurred frequently in patients treated with losartan potassium and hydrochlorothiazide tablets alone, but were rarely of clinical importance. No patients were discontinued due to anemia.

Liver Function Tests:

Occasional elevations of liver enzymes and/or serum bilirubin have occurred. In patients with essential hypertension treated with losartan potassium and hydrochlorothiazide tablets alone, no patients were discontinued due to these laboratory adverse experiences.

Serum Electrolytes:

See PRECAUTIONS.

HOW SUPPLIED

Losartan Potassium and Hydrochlorothiazide Tablets, USP 50 mg/ 12.5 mg, are white to off-white, capsule-shaped, film-coated tablets debossed with "ZD18" on one side and plain on other side and are supplied as follows:

NDC 68382-142-06 in bottle of 30 tablets

NDC 68382-142-16 in bottle of 90 tablets

NDC 68382-142-10 in bottle of 1000 tablets

NDC 68382-142-40 in bottle of 5000 tablets

Losartan Potassium and Hydrochlorothiazide Tablets, USP 100 mg/ 25 mg, are white to off-white, capsule-shaped, film-coated tablets debossed with "ZD19" on one side and plain on other side and are supplied as follows:

NDC 68382-143-06 in bottle of 30 tablets

NDC 68382-143-16 in bottle of 90 tablets

NDC 68382-143-10 in bottle of 1000 tablets

NDC 68382-143-23 in bottle of 4000 tablets

Storage:

Store at 20° to 25°C (68° to 77°F) [See USP Controlled Room Temperature]. Keep container tightly closed. Protect from light.

Dispense in a tight, light-resistant container.

Patient Information Leaflet

Read the Patient Information that comes with losartan potassium and hydrochlorothiazide tablets before you start taking it and each time you get a refill. There may be new information. This leaflet does not take the place of talking with your doctor about your condition and treatment.

What is the most important information I should know about losartan potassium and hydrochlorothiazide tablets?

Do not take losartan potassium and hydrochlorothiazide tablets if you are pregnant or plan to become pregnant. Losartan potassium and hydrochlorothiazide tablets can harm your unborn baby causing injury and even death. Stop taking losartan potassium and hydrochlorothiazide tablets if you become pregnant and call your doctor right away. If you plan to become pregnant, talk to your doctor about other treatment options before taking losartan potassium and hydrochlorothiazide tablets.

What is losartan potassium and hydrochlorothiazide tablet?

Losartan potassium and hydrochlorothiazide tablet contains 2 prescription medicines, an angiotensin receptor blocker (ARB) and a diuretic (water pill). It is used to:

- lower high blood pressure (hypertension). Losartan potassium and hydrochlorothiazide tablets are not usually the first medicine used to treat high blood pressure.
- lower the chance of stroke in patients with high blood pressure and a heart problem called left ventricular hypertrophy (LVH). Losartan potassium and hydrochlorothiazide tablets may not help Black patients with this problem.

Losartan potassium and hydrochlorothiazide tablets have not been studied in children less than 18 years old.

High Blood Pressure (hypertension) Blood pressure is the force in your blood vessels when your heart beats and when your heart rests. You have high blood pressure when the force is too much. The losartan ingredient in losartan potassium and hydrochlorothiazide tablet can help your blood vessels relax so your blood pressure is lower. The hydrochlorothiazide ingredient in losartan potassium and hydrochlorothiazide tablet works by making your kidneys pass more water and salt.

Left Ventricular Hypertrophy (LVH) is an enlargement of the walls of the left chamber of the heart (the heart’s main pumping chamber). LVH can happen from several things. High blood pressure is the most common cause of LVH.

Who should not take losartan potassium and hydrochlorothiazide tablets?

Do not take losartan potassium and hydrochlorothiazide tablets if you:

- are allergic to any ingredients in losartan potassium and hydrochlorothiazide tablets. See a complete list of Ingredients in losartan potassium and hydrochlorothiazide tablets at the end of this leaflet.
- are allergic to any sulfonamide-containing ("sulfa") medicines. Ask your doctor if you are not sure what sulfonamide-containing ("sulfa") medicines are.
- are not passing urine

What should I tell my doctor before taking losartan potassium and hydrochlorothiazide tablets?

Tell your doctor about all your medical conditions including if you:

- are pregnant or planning to become pregnant. See "What is the most important information I should know about losartan potassium and hydrochlorothiazide tablets?"
- are breast-feeding or plan to breast-feed. Losartan potassium and hydrochlorothiazide can pass into your milk and may harm your baby. You and your doctor should decide if you will take losartan potassium and hydrochlorothiazide tablets or breast-feed. You should not do both.
- have been vomiting (throwing up), having diarrhea, sweating a lot, or not drinking enough fluids. These could cause you to have low blood pressure.
- have liver problems
- have kidney problems
- have systemic lupus erythematosus (Lupus; SLE)
- have diabetes
- have asthma
- have gout
- have any allergies

Tell your doctor about all of the medicines you take, including prescription and non-prescription medicines, vitamins, and herbal supplements.

Losartan potassium and hydrochlorothiazide tablets and certain other medicines may interact with each other. Especially tell your doctor if you are taking:

- potassium supplements
- salt substitutes containing potassium
- water pills (diuretics)
- lithium (a medicine used to treat a certain kind of depression)
- medicines used to treat pain and arthritis, called non-steroidal anti-inflammatory drugs (NSAIDs), including COX-2 inhibitors.

Know the medicines you take. Keep a list of your medicines and show it to your doctor and pharmacist when you get a new medicine.

How should I take losartan potassium and hydrochlorothiazide tablets??

- Take losartan potassium and hydrochlorothiazide tablets exactly as prescribed by your doctor. Your doctor may change your dose if needed.
- Losartan potassium and hydrochlorothiazide tablets can be taken with or without food.
- If you miss a dose, take it as soon as you remember. If it is close to your next dose, do not take the missed dose. Just take the next dose at your regular time.
- If you take too much losartan potassium and hydrochlorothiazide tablets, call your doctor or Poison Control Center, or go to the nearest hospital emergency room right away.
- Your doctor may do blood tests from time to time while you are taking losartan potassium and hydrochlorothiazide tablets.

What are the possible side effects of losartan potassium and hydrochlorothiazide tablets?

Losartan potassium and hydrochlorothiazide tablets may cause the following side effects that may be serious:

- injury or death of unborn babies. See "What is the most important information I should know about losartan potassium and hydrochlorothiazide tablets?"
- allergic reaction. Symptoms of an allergic reaction are swelling of the face, lips, throat, or tongue. Get emergency medical help right away and stop taking losartan potassium and hydrochlorothiazide tablets.
- low blood pressure (hypotension). Low blood pressure may cause you to feel faint or dizzy. Lie down if you feel faint or dizzy. Call your doctor right away.
- a new or worsening condition called systemic lupus erythematosus (Lupus; SLE)
- if you have kidney problems, you may see a worsening in how well your kidneys work. Call your doctor if you get swelling in your feet, ankles, or hands, or unexplained weight gain.
- If you have liver problems, you may see a worsening in how well your liver works. Call your doctor if you get nausea, pain in the right upper stomach area (abdomen), yellow eyes or skin (which can be itchy).

The most common side effects of losartan potassium and hydrochlorothiazide tablets in people with high blood pressure are:

- "colds" (upper respiratory infection)
- dizziness
- stuffy nose
- back pain
- fast or irregular heartbeat (palpitations)
- rash

Tell your doctor if you get any side effect that bothers you or that won’t go away. This is not a complete list of side effects. For a complete list, ask your doctor or pharmacist.

How should I store losartan potassium and hydrochlorothiazide tablets?

- Store losartan potassium and hydrochlorothiazide tablets at room temperature at 20° to 25°C (68° to 77°F).
- Keep losartan potassium and hydrochlorothiazide tablets in a tightly closed container, and keep losartan potassium and hydrochlorothiazide tablets out of the light.
- Keep losartan potassium and hydrochlorothiazide tablets and all medicines out of the reach of children.

General information about losartan potassium and hydrochlorothiazide tablets

Medicines are sometimes prescribed for conditions that are not mentioned in patient information leaflets. Do not use losartan potassium and hydrochlorothiazide tablets for a condition for which it was not prescribed. Do not give losartan potassium and hydrochlorothiazide tablets to other people, even if they have the same symptoms that you have. It may harm them.

This leaflet summarizes the most important information about losartan potassium and hydrochlorothiazide tablets. If you would like more information, talk with your doctor. You can ask your pharmacist or doctor for information that is written for health professionals.

Manufactured by:

Cadila Healthcare Ltd.

Ahmedabad, India

Distributed by:

Zydus Pharmaceuticals USA Inc.

Pennington, NJ 08534

PRINCIPAL DISPLAY PANEL

NDC 68258-6040-XX
NDC 68258-6040-03
NDC 68258-6040-09